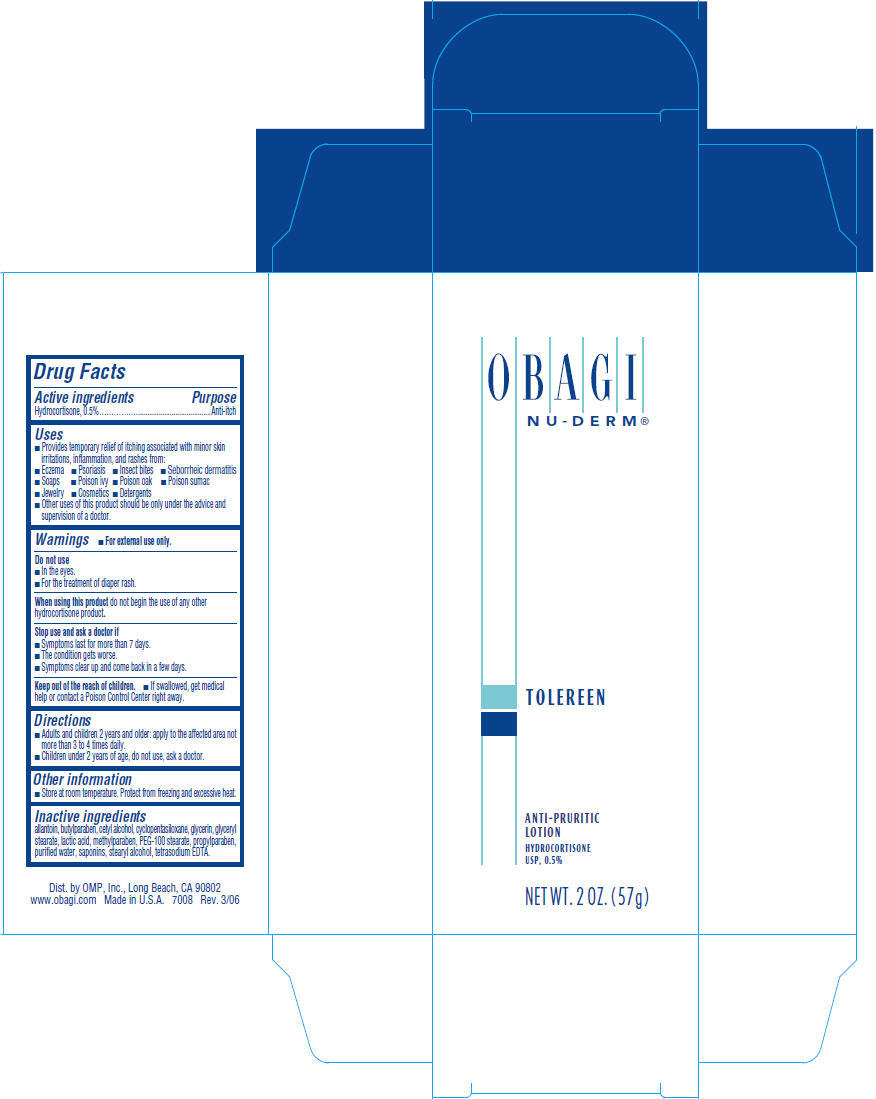 DRUG LABEL: NU-DERM Tolereen 
NDC: 62032-112 | Form: LOTION
Manufacturer: OMP, Inc.
Category: otc | Type: HUMAN OTC DRUG LABEL
Date: 20111026

ACTIVE INGREDIENTS: Hydrocortisone 5 mg/1 g
INACTIVE INGREDIENTS: STEARYL ALCOHOL; CYCLOMETHICONE 5; GLYCERYL MONOSTEARATE; PEG-100 STEARATE; CETYL ALCOHOL; GLYCERIN; LACTIC ACID; METHYLPARABEN; ALLANTOIN; PROPYLPARABEN; EDETATE SODIUM; BUTYLPARABEN; WATER

OBAGI
NU-DERM®
TOLEREEN

Drug Facts

Active ingredients

Hydrocortisone, 0.5%

Purpose

Anti-itch

Uses

- Provides temporary relief of itching associated with minor skin irritations, inflammation, and rashes from:
  - Eczema
  - Psoriasis
  - Insect bites
  - Seborrheic dermatitis
  - Soaps
  - Poison ivy
  - Poison oak
  - Poison sumac
  - Jewelry
  - Cosmetics
  - Detergents
- Other uses of this product should be only under the advice and supervision of a doctor.

Warnings

- For external use only.

Do not use

- In the eyes.
- For the treatment of diaper rash.

When using this product do not begin the use of any other hydrocortisone product.

Stop use and ask a doctor if

- Symptoms last for more than 7 days.
- The condition gets worse.
- Symptoms clear up and come back in a few days.

Keep out of the reach of children.

- If swallowed, get medical help or contact a Poison Control Center right away.

Directions

- Adults and children 2 years and older: apply to the affected area not more than 3 to 4 times daily.
- Children under 2 years of age, do not use, ask a doctor.

Other information

- Store at room temperature. Protect from freezing and excessive heat.

Inactive ingredients

allantoin, butylparaben, cetyl alcohol, cyclopentasiloxane, glycerin, glyceryl stearate, lactic acid, methylparaben, PEG-100 stearate, propylparaben, purified water, saponins, stearyl alcohol, tetrasodium EDTA.

Dist. by OMP, Inc., Long Beach, CA 90802

PRINCIPAL DISPLAY PANEL - 57g Bottle Carton

OBAGI
NU-DERM®

TOLEREEN

ANTI-PRURITIC
LOTION

HYDROCORTISONE
USP, 0.5%

NET WT. 2 OZ. (57g)